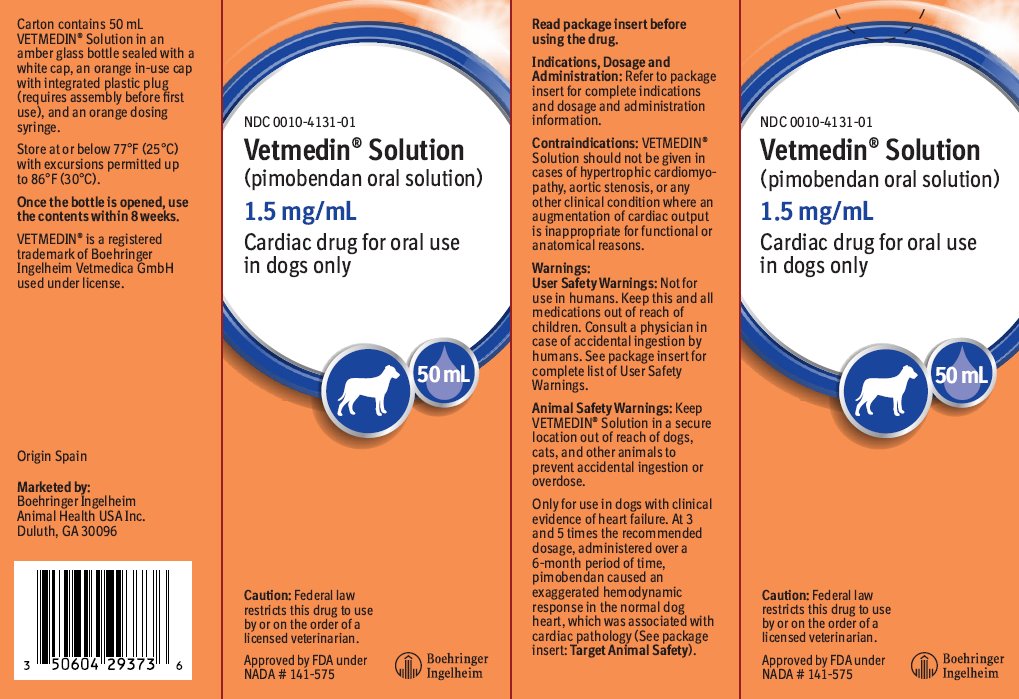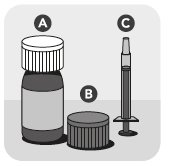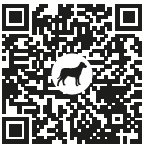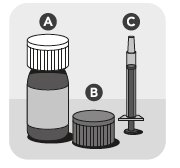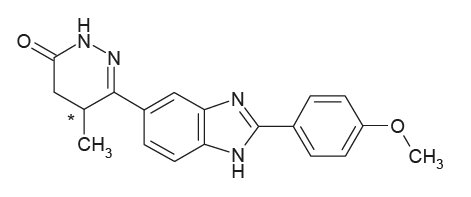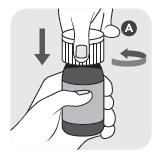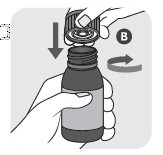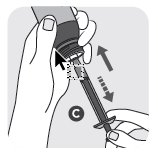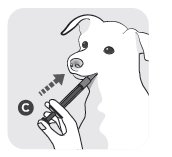 DRUG LABEL: Vetmedin Solution
NDC: 0010-4131 | Form: SOLUTION
Manufacturer: Boehringer Ingelheim Animal Health USA Inc.
Category: animal | Type: PRESCRIPTION ANIMAL DRUG LABEL
Date: 20241028

ACTIVE INGREDIENTS: PIMOBENDAN 1.5 mg/1 mL

Vetmedin® Solution
(pimobendan oral solution)

1.5 mg/mL

Cardiac drug for oral use in dogs only

Caution:

Federal law restricts this drug to use by or on the order of a licensed veterinarian.

Description:

VETMEDIN® Solution (pimobendan oral solution) is a clear to yellow to slightly green to slightly brown aqueous solution containing 1.5 mg/mL pimobendan. Pimobendan, a benzimidazole-pyridazinone derivative, is a non-sympathomimetic, non-glycoside inotropic drug with vasodilatative properties. The chemical name of pimobendan is 4,5-dihydro-6-[2-(4-methoxyphenyl)-1H-benzimidazole-5-yl]-5-methyl-3(2H)-pyridazinone.

The structural formula of pimobendan is:

Indications:

VETMEDIN Solution (pimobendan oral solution) is indicated for the management of the signs of mild, moderate, or severe congestive heart failure in dogs due to clinical myxomatous mitral valve disease (MMVD) or dilated cardiomyopathy (DCM). VETMEDIN Solution is indicated for use with concurrent therapy for congestive heart failure (e.g., furosemide, etc.) as appropriate on a case-by-case basis.

Dosage and Administration:

Always provide the Client Information Sheet to the dog owner with each prescription.

VETMEDIN Solution should be administered orally at a total daily dose of 0.23 mg/lb (0.5 mg/kg) body weight. The total daily dose should be divided into 2 equal portions administered approximately 12 hours apart (i.e., morning and evening).

The syringe is calibrated to deliver the appropriate morning or evening dose when drawn to the dog’s nearest weight in pounds.

VETMEDIN Solution should be administered directly into the mouth. Do not mix into food.

VETMEDIN Solution includes an amber glass bottle sealed with a white cap (A), an orange cap with integrated plastic plug (B), and an orange dosing syringe (C).

Do not shake the bottle before or during use to avoid foaming.

VETMEDIN Solution should be administered using the orange dosing syringe provided in the package. At the time of first use, the white cap should be removed and discarded. Once the orange cap has been screwed onto the bottle and the integrated plastic plug is in place, the dosing syringe fits onto the plug. The dosing syringe has 1 pound incremental marks. Each dose should be rounded to the nearest 1 pound increment (e.g., a dose for a dog 5.5 lb or greater should be rounded up to 6 lb).

An in-use video demonstration can be found using the URL https://go.boehringer.com/q7lKE or the QR code below.

Close the bottle tightly using the orange cap. After administration, clean the outside of the syringe by wiping with a clean, dry cloth or tissue after each use. If the syringe clogs, rinse without removing the plunger by using water and wiping the outside of the syringe dry with a clean cloth or tissue.

Contraindications:

VETMEDIN Solution should not be given in cases of hypertrophic cardiomyopathy, aortic stenosis, or any other clinical condition where an augmentation of cardiac output is inappropriate for functional or anatomical reasons.

Warnings:

User Safety Warnings: Not for use in humans. Keep this and all medications out of reach of children. Consult a physician in case of accidental ingestion by humans.

Wash hands after use. This product may cause eye irritation. Avoid contact with eyes. In case of contact, flush affected eye(s) immediately and thoroughly with water. If wearing contact lenses, flush the eyes first with water and then remove the lens(es) and continue to flush thoroughly with water. If eye irritation continues, seek medical advice and provide this product information to the physician.

Exposure to product may induce a local or systemic allergic reaction in sensitized individuals.

Animal Safety Warnings: Keep VETMEDIN Solution in a secure location out of reach of dogs, cats, and other animals to prevent accidental ingestion or overdose.

Only for use in dogs with clinical evidence of heart failure. At 3 and 5 times the recommended dosage, administered over a 6-month period of time, pimobendan caused an exaggerated hemodynamic response in the normal dog heart, which was associated with cardiac pathology (See Target Animal Safety).

Precautions:

The safety of VETMEDIN Solution has not been established in dogs with asymptomatic heart disease or in heart failure caused by etiologies other than MMVD or DCM. The safe use of VETMEDIN Solution has not been evaluated in dogs younger than 6 months of age, dogs with congenital heart defects, dogs with diabetes mellitus or other serious metabolic diseases, dogs used for breeding, or pregnant or lactating bitches.

Adverse Reactions:

The safety and effectiveness of VETMEDIN Solution was established by demonstrating bioequivalence with VETMEDIN Chewable Tablets. (See Clinical Pharmacology).

Pre-Approval Experience: Clinical findings/adverse reactions were recorded in a 56-day field study of dogs with congestive heart failure (CHF) due to MMVD (256 dogs) or DCM (99 dogs). Dogs were treated with either VETMEDIN Chewable Tablets (175 dogs) or the active control enalapril maleate (180 dogs). Dogs in both treatment groups received additional background cardiac therapy (See Effectiveness for details and the difference in digoxin administration between treatment groups).

The VETMEDIN Chewable Tablets group had the following prevalence (percent of dogs with at least one occurrence) of common adverse reactions/new clinical findings (not present in a dog prior to beginning study treatments): poor appetite (38%), lethargy (33%), diarrhea (30%), dyspnea (29%), azotemia (14%), weakness and ataxia (13%), pleural effusion (10%), syncope (9%), cough (7%), sudden death (6%), ascites (6%), and heart murmur (3%). Prevalence was similar in the active control group.

The prevalence of renal failure was higher in the active control group (4%) compared to the VETMEDIN Chewable Tablets group (1%).

Adverse reactions/new clinical findings were seen in both treatment groups and were potentially related to CHF, the therapy of CHF, or both. The following adverse reactions/new clinical findings are listed according to body system and are not in order of prevalence:

CHF death, sudden death, chordae tendineae rupture, left atrial tear, arrhythmias overall, tachycardia, syncope, weak pulses, irregular pulses, increased pulmonary edema, dyspnea, increased respiratory rate, coughing, gagging, pleural effusion, ascites, hepatic congestion, decreased appetite, vomiting, diarrhea, melena, weight loss, lethargy, depression, weakness, collapse, shaking, trembling, ataxia, seizures, restlessness, agitation, pruritus, increased water consumption, increased urination, urinary accidents, azotemia, dehydration, abnormal serum electrolyte, protein, and glucose values, mild increases in serum hepatic enzyme levels, and mildly decreased platelet counts.

See Table 1 for mortality due to CHF (including euthanasia, natural death, and sudden death) and for the development of new arrhythmias (not present in a dog prior to beginning study treatments) by treatment group and type of heart disease (MMVD or DCM) in the 56-day field study.

Table 1: CHF Death and New Arrhythmias in the 56-Day Field Study

 | VETMEDIN Chewable Tablets Group | Active Control Group
Dogs that died due to CHF | 14.3%; n = 175 | 14.4%; n = 180
Dogs that died due to CHF | 9 of 126 dogs with MMVD | 16 of 130 dogs with MMVD
Dogs that died due to CHF | 16 of 49 dogs with DCM | 10 of 50 dogs with DCM
Dogs that developed new arrhythmiasa | 39.4%; n = 175 | 45.0%; n = 180
Dogs that developed new arrhythmiasa | 45 of 126 dogs with MMVD | 59 of 130 dogs with MMVD
Dogs that developed new arrhythmiasa | 24 of 49 dogs with DCM | 22 of 50 dogs with DCM

a New arrhythmias included supraventricular premature beats and tachycardia, atrial fibrillation, atrioventricular block, sinus bradycardia, ventricular premature beats and tachycardia, and bundle branch block.

Following the 56-day masked field study, 137 dogs in the VETMEDIN Chewable Tablets group were allowed to continue on VETMEDIN Chewable Tablets in an open-label extended-use study without restrictions on concurrent therapy. The adverse reactions/new clinical findings in the extended-use study were consistent with those reported in the 56-day study, with the following exception: One dog in the extended-use study developed acute cholestatic liver failure after 140 days on VETMEDIN Chewable Tablets and furosemide.

Post-Approval Experience (2023):

The following adverse events are based on post-approval adverse drug experience reporting for VETMEDIN Chewable Tablets. Not all adverse events are reported to FDA/CVM. It is not always possible to reliably estimate the adverse event frequency or establish a causal relationship to product exposure using these data.

The following adverse events reported in dogs are listed in decreasing order of reporting frequency:

Diarrhea, lethargy, anorexia, emesis, cough, tachycardia, ataxia, dyspnea, convulsion, elevated liver enzymes (ALT, ALP), increased BUN and/or creatinine, tremors, hyperactivity, pruritus, syncope, allergic reactions (including allergic edema/facial edema, erythema, and hives), hypotension, hypertension, coagulation abnormalities (including thrombocytopenia, hemorrhage and petechia), and hyperglycemia (with or without diabetes mellitus).

Death has been reported in some cases.

Contact Information:

To report suspected adverse reactions, to obtain a Safety Data Sheet (SDS), or for technical assistance, contact Boehringer Ingelheim Animal Health USA Inc. at 1-888-637-4251. For additional information about adverse drug experience reporting for animal drugs, contact the FDA at 1-888-FDA-VETS or at https://www.fda.gov/reportanimalae.

Information for Dog Owners:

Always provide the Client Information Sheet with each prescription and review it with the dog owner or person responsible for care of the dog. Advise dog owners about signs of disease progression and possible adverse reactions with use of VETMEDIN Solution.

Clinical Pharmacology:

Mechanism of Action: Pimobendan exerts a stimulatory myocardial effect by a dual mechanism of action consisting of an increase in calcium sensitivity of cardiac myofilaments and inhibition of phosphodiesterase (Type III). Pimobendan exhibits vasodilating activity by inhibiting phosphodiesterase III activity.

Pharmacodynamics: In normal dogs instrumented with left ventricular (LV) pressure transducers, pimobendan increased LV dP/dtmax (a measure of contractility of the heart) in a dose dependent manner between 0.1 and 0.5 mg/kg orally. The effect was still present 8 hours after dosing. There was a delay between peak blood levels of pimobendan and active metabolite and the maximum physiologic response (peak LV dP/dtmax). Blood levels of pimobendan and active metabolite began to drop before maximum contractility was seen. Repeated oral administration of pimobendan did not result in evidence of tachyphylaxis (decreased positive inotropic effect) or drug accumulation (increased positive inotropic effect). Laboratory studies indicate that the positive inotropic effect of pimobendan may be attenuated by the concurrent use of a β-adrenergic blocker or a calcium channel blocker.

Pharmacokinetics: VETMEDIN Solution was compared to VETMEDIN Chewable Tablets in a randomized, masked, four-period, two-sequence single-dose full replicative cross-over bioequivalence study. Twenty-four Beagle dogs (12 male/12 female), ranging in age from 1 to 10 years and weighing between 9.0 and 16.5 kg at enrollment were administered a 5 mg total dose of VETMEDIN Solution and VETMEDIN Chewable Tablets on two separate occasions. Using the mixed scaling approach, reference-scaled average bioequivalence (RSABE) was demonstrated. Mean pharmacokinetic parameters from this study are provided in Table 2.

Table 2: Arithmetic mean (± standard deviation) pimobendan plasma pharmacokinetic parameters after a 5 mg (0.29 – 0.41 mg/kg) oral administration of VETMEDIN Solution to male and female Beagle dogs in a laboratory bioequivalence study.

Parameter | Estimate | N
Cmax (ng/mL) | 24.0 ± 18.3 | 48
Tmaxa (h) | 0.75 (0.25 – 3) | 48
AUClast (h*ng/mL) | 38.8 ± 26.2 | 48
AUCinf (h*ng/mL) | 39.0 ± 26.5 | 47
t½ (h) | 0.9 ± 0.4 | 47

aMedian (Range)

Cmax =maximum plasma concentration

Tmax = time to maximum plasma concentration

AUClast = area under the curve from the time of dosing to the last quantifiable plasma concentration

AUCinf = area under the curve from the time of dosing extrapolated to infinity

t½ = half-life

N = observations

The bioequivalence study also demonstrated similar AUC and Cmax of the active metabolite between VETMEDIN Solution and VETMEDIN Chewable Tablets. Pimobendan is oxidatively demethylated to a pharmacologically active metabolite, which is then conjugated with sulfate or glucuronic acid and excreted mainly via feces.

The AUClast of VETMEDIN Solution is 37% lower and the Cmax is 39% lower in the fed state compared to the fasted state (N=12 dogs). Statistical comparisons, where appropriate, were made using natural log transformed data and geometric means.

Effectiveness:

The effectiveness of VETMEDIN Solution was established by demonstrating bioequivalence with VETMEDIN Chewable Tablets. (See Clinical Pharmacology).

In a double-masked, multi-site, 56-day field study, 355 dogs with modified New York Heart Association‡ (NYHA) Class II, III, or IV CHF due to MMVD or DCM were randomly assigned to either the active control (enalapril maleate) or the VETMEDIN Chewable Tablets treatment group. Of the 355 dogs, 52% were male and 48% were female; 72% were diagnosed with MMVD and 28% were diagnosed with DCM; 34% had Class II, 47% had Class III, and 19% had Class IV CHF. Dogs ranged in age and weight from 1 to 17 years and 3.3 to 191 lbs, respectively. The most common breeds were mixed breed, Doberman Pinscher, Cocker Spaniel, Miniature/Toy Poodle, Maltese, Chihuahua, Miniature Schnauzer, Dachshund, and Cavalier King Charles Spaniel. The 180 dogs (130 MMVD, 50 DCM) in the active control group received enalapril maleate (0.5 mg/kg once or twice daily), and all but 2 received furosemide. Per protocol, all dogs with DCM in the active control group received digoxin. The 175 dogs (126 MMVD, 49 DCM) in the VETMEDIN Chewable Tablets group received pimobendan (0.5 mg/kg/day divided into 2 portions that were not necessarily equal, and the portions were administered approximately 12 hours apart), and all but 4 received furosemide. Digoxin was optional for treating supraventricular tachyarrhythmia in either treatment group, as was the addition of a β-adrenergic blocker if digoxin was ineffective in controlling heart rate. After initial treatment at the clinic on Day 1, dog owners were to administer the assigned product and concurrent medications for up to 56±4 days.

The determination of effectiveness (treatment success) for each case was based on improvement in at least 2 of the 3 following primary variables: modified NYHA classification, pulmonary edema score by a masked veterinary radiologist, and the investigator’s overall clinical effectiveness score (based on physical examination, radiography, electrocardiography, and clinical pathology). Attitude, pleural effusion, coughing, activity level, furosemide dosage change, cardiac size, body weight, survival, and owner observations were secondary evaluations contributing information supportive to product effectiveness and safety.

Based on protocol compliance and individual case integrity, 265 cases (134 VETMEDIN Chewable Tablets, 131 active control) were evaluated for treatment success on Day 29. See Table 3 for effectiveness results.

Table 3: Effectiveness Results for the 56-Day Field Study

 | VETMEDIN Chewable Tablets Group | Active Control Group
Treatment Success on; Day 29 | 80.7%; n = 134 | 76.3%; n = 131
Treatment Success on; Day 29 | 88 of 101 dogs with MMVD | 77 of 100 dogs with MMVD
Treatment Success on; Day 29 | 20 of 33 dogs with DCM | 23 of 31 dogs with DCM
Treatment Success on; Day 56 | 71.1%; n = 113 | 67.2%; n = 110
Treatment Success on; Day 56 | 66 of 85 dogs with MMVD | 56 of 85 dogs with MMVD
Treatment Success on; Day 56 | 13 of 28 dogs with DCM | 17 of 25 dogs with DCM
No increase in furosemide dose between Day 1 and Day 29 | 78.3%; n = 130 | 68.6%; n = 126

At the end of the 56-day study, dogs in the VETMEDIN Chewable Tablets group were enrolled in an unmasked field study to monitor safety under extended use, without restrictions on concurrent medications.

VETMEDIN Chewable Tablets were used safely in dogs concurrently receiving furosemide, digoxin, enalapril, atenolol, spironolactone, nitroglycerin, hydralazine, diltiazem, antiparasitic products (including heartworm disease prevention), antibiotics (metronidazole, cephalexin, amoxicillin-clavulanate, fluoroquinolones), topical ophthalmic and otic products, famotidine, theophylline, levothyroxine sodium, diphenhydramine, hydrocodone, metoclopramide, and butorphanol, and in dogs on sodium-restricted diets.

‡ The modified NYHA classification was historically used to stage dogs with heart disease.

A dog with modified NYHA Class II heart failure has fatigue, shortness of breath, coughing, etc. apparent when ordinary exercise is exceeded.

A dog with modified NYHA Class III heart failure is comfortable at rest, but exercise capacity is minimal.

A dog with modified NYHA Class IV heart failure has no capacity for exercise and disabling clinical signs are present even at rest.

Target Animal Safety:

The safety of VETMEDIN Solution was established by demonstrating bioequivalence with VETMEDIN Chewable Tablets. (See Clinical Pharmacology).

In a laboratory study, VETMEDIN Chewable Tablets were administered to 6 healthy Beagles per treatment group at 0 (control), 1, 3, and 5 times the recommended dosage for 6 months. See Table 4 for cardiac pathology results. The cardiac pathology/histopathology noted in the 3X and 5X dose groups is typical of positive inotropic and vasodilator drug toxicity in normal dog hearts, and is associated with exaggerated hemodynamic responses to these drugs. None of the dogs developed signs of heart failure and there was no mortality.

Table 4: Incidence of Cardiac Pathology/Histopathology in the Six-month Safety Study

Severe left ventricular hypertrophy with; multifocal subendocardial ischemic lesions | One 3X and two 5X dogsa
Moderate to marked myxomatous thickening of the mitral valves | Three 5X dogs
Myxomatous thickening of the chordae; tendineae | One 3X and two 5X dogs
Endocardial thickening of the left ventricular outflow tract | One 1X, two 3X, and two 5X dogs
Left atrial endocardial thickening (jet lesions) in 2 of the dogs that developed murmurs of mitral valve insufficiency | One 3X and one 5X dog
Granulomatous inflammatory lesion; in the right atrial myocardium | One 3X dog

aMost of the gross and histopathologic findings occurred in these three dogs

Murmurs of mitral valve insufficiency were detected in one 3X (Day 65) and two 5X dogs

(Days 135 and 163). These murmurs (grades II-III of VI) were not associated with clinical signs.

Indirect blood pressure was unaffected by VETMEDIN Chewable Tablets at the label dose (1X). Mean diastolic blood pressure was decreased in the 3X group (74 mmHg) compared to the control group (82 mmHg). Mean systolic blood pressure was decreased in the 5X group (117 mmHg) compared to the control group (124 mmHg). None of the dogs had clinical signs of hypotension.

On 24-hour Holter monitoring, mean heart rate was increased in the 5X group (101 beats/min) compared to the control group (94 beats/min). Not counting escape beats, the 3X and 5X groups had slightly higher numbers of isolated ventricular ectopic complexes (VEs). The maximum number of non-escape VEs recorded either at baseline or in a control group dog was 4 VEs/24 hours. At either Week 4 or Week 20, three 3X group dogs had maximums of 33, 13, and 10 VEs/24 hours, and two 5X group dogs had maximums of 22 and 9 VEs/24 hours. One 1X group dog with no VEs at baseline had 6 VEs/24 hours at Week 4 and again at Week 20. Second-degree atrioventricular heart block was recorded in one 3X group dog at Weeks 4 and 20, and in one dog from each of the 1X and 5X groups at Week 20. None of the dogs had clinical signs associated with these electrocardiogram changes.

Treatment was associated with small differences in mean platelet counts (decreased in the 3X and 1X groups), potassium (increased in the 5X group), glucose (decreased in the 1X and 3X groups), and maximum blood glucose in glucose curves (increased in the 5X group).

All individual values for these variables were within the normal range. Three 1X and one 5X group dogs had mild elevations of alkaline phosphatase (less than two times normal).

Loose stools and vomiting were infrequent and self-limiting.

Storage Information:

Store at or below 77°F (25°C) with excursions permitted up to 86°F (30°C). Once the bottle is opened, use the contents within 8 weeks.

How Supplied:

VETMEDIN Solution (pimobendan oral solution): Available as 1.5 mg/mL, 50 mL fill volume, is supplied in a 60 mL amber glass bottle sealed with a white cap, an orange in-use cap with integrated plastic plug, and an orange dosing syringe.

NDC 0010-4131-01

Approved by FDA under NADA # 141-575

Marketed by:

Boehringer Ingelheim Animal Health USA Inc.

Duluth, GA 30096

VETMEDIN® is a registered trademark of Boehringer Ingelheim Vetmedica GmbH used under license.

© 2023 Boehringer Ingelheim Animal Health USA Inc. All rights reserved.

Revised 12/2023

Client Information Sheet

Vetmedin® Solution

(pimobendan oral solution)

1.5 mg/mL

Cardiac drug for oral use in dogs only

The Client Information Sheet contains important information about VETMEDIN® Solution

(pimobendan oral solution). You should read this information before you start giving VETMEDIN Solution and review it each time the prescription is refilled as there may be new information. This sheet does not take the place of instructions from your veterinarian. Talk with your veterinarian if you do not understand any of this information or if you want to know more about VETMEDIN Solution.

What is VETMEDIN Solution?

VETMEDIN Solution is used to manage the signs of congestive heart failure in dogs.

What should I tell my veterinarian about my dog before starting VETMEDIN Solution?

- Tell your veterinarian about other medications your pet is taking, including prescription drugs, over the counter drugs, heartworm preventives, flea & tick products, and vitamins and supplements, including herbal medications.
- Tell your veterinarian if your dog is pregnant, nursing, or you intend to breed him/her.
- Tell your veterinarian if your dog has any other serious health conditions.
- Tell your veterinarian if your dog has or develops any signs of disease progression, such as labored breathing, increased resting respiratory rates, fainting, abnormal heart rhythms, and coughing.

Talk to your veterinarian about the risks and benefits of giving VETMEDIN Solution to your dog.

What are some of the possible side effects of VETMEDIN Solution?

VETMEDIN Solution may cause side effects, even at the prescribed dose. Contact your veterinarian immediately if your dog develops a serious or concerning medical problem or side effect while taking VETMEDIN Solution.

The most common side effects reported in dogs treated with VETMEDIN Chewable Tablets are poor appetite, lack of energy (lethargy), diarrhea, and difficulty breathing (dyspnea).

To report a suspected adverse reaction (side effect), to obtain a Safety Data Sheet (SDS), or for technical assistance, contact Boehringer Ingelheim Animal Health USA Inc. at 1-888-637-4251.

For additional information about reporting side effects for animal drugs, contact FDA at 1-888-FDA-VETS or https://www.fda.gov/reportanimalae.

How do I give VETMEDIN Solution to my dog?

VETMEDIN Solution should be given to your dog directly in their mouth (orally) twice a day, about 12 hours apart. Do not mix into food.

Follow your veterinarian’s instructions for how much VETMEDIN Solution to give your dog. Because the dose is based on body weight, the dose you are prescribed to give your dog may be rounded to the nearest pound weight mark on the dosing syringe.

Your package of VETMEDIN Solution includes an amber glass bottle sealed with a white cap (A), an orange cap with integrated plastic plug (B), and an orange dosing syringe (C).

Do not shake the bottle before or during use to avoid foaming.

Give VETMEDIN Solution using the orange dosing syringe provided in the package. The dosing syringe fits onto the plug and has 1 pound marks to use for measuring the dose.

Please read the following instructions carefully prior to first use of VETMEDIN Solution.

A video demonstration can also be found using the URL https://go.boehringer.com/q7lKE or the QR code below.

At the time of first use

1) Open bottle in an upright position by pressing down on the white child resistant cap (A) and simultaneously turning the cap counterclockwise. Discard the white cap (A).

2) Close the bottle with the orange cap (B) by turning the cap clockwise. The orange cap contains a plastic plug which should automatically attach to the bottle opening. Ensure the cap is tightly closed to appropriately insert plug into the top of the bottle.

To dose your dog

3) Remove the orange cap (B) from the bottle by pressing down on the orange child resistant cap and simultaneously turning the cap counterclockwise. Gently push the end of the orange dosing syringe (C) onto the plug. Turn the bottle and syringe upside down. Pull the plunger out and fill the dosing syringe to the dose weight prescribed by your veterinarian. Turn the bottle upright and remove the dosing syringe from the bottle. Replace the orange cap (B) onto the bottle and close tightly.

4) Put the end of the dosing syringe (C) into your dog´s mouth and push the plunger to give the prescribed dose.
5) After dosing, clean the outside of the syringe by wiping with a clean, dry cloth or tissue after each use. If the syringe clogs, rinse without removing the plunger by using water and wiping the outside of the syringe dry with a clean cloth or tissue.

If your dog vomits after being given VETMEDIN Solution, please contact your veterinarian. Unless directed otherwise, do not give additional VETMEDIN Solution again until the next scheduled dose.

What if my dog receives more VETMEDIN Solution than what is prescribed?

Contact your veterinarian as soon as possible.

What else should I know about VETMEDIN Solution?

VETMEDIN Solution is not for use in humans. Keep this and all medications out of reach of children.

Wash hands after use. This product may cause eye irritation. Avoid contact with eyes. In case of contact, flush affected eye(s) immediately and thoroughly with water. If wearing contact lenses, flush the eyes first with water and then remove the lens(es) and continue to flush thoroughly with water. If eye irritation continues, seek medical advice and provide this product information to the physician.

Consult a physician in case of accidental ingestion by humans. It is important to show the treating physician a copy of the package insert, label, or this client information sheet. VETMEDIN Solution is a non-sympathomimetic, non-glycoside inotropic drug with vasodilatative properties.

This client information sheet contains a summary of important information about VETMEDIN Solution. For more detailed information about VETMEDIN Solution, talk with your veterinarian.

How should I store VETMEDIN Solution?

VETMEDIN Solution should be stored at room temperature at or below 77°F (25°C). Temperatures as high as 86°F (30°C) can be acceptable for short periods of time. Do not shake. Once the bottle is opened, use the contents within 8 weeks.

Keep VETMEDIN Solution in a secure location out of reach of dogs, cats, and other animals to prevent accidental ingestion or overdose.

Revised 12/2023